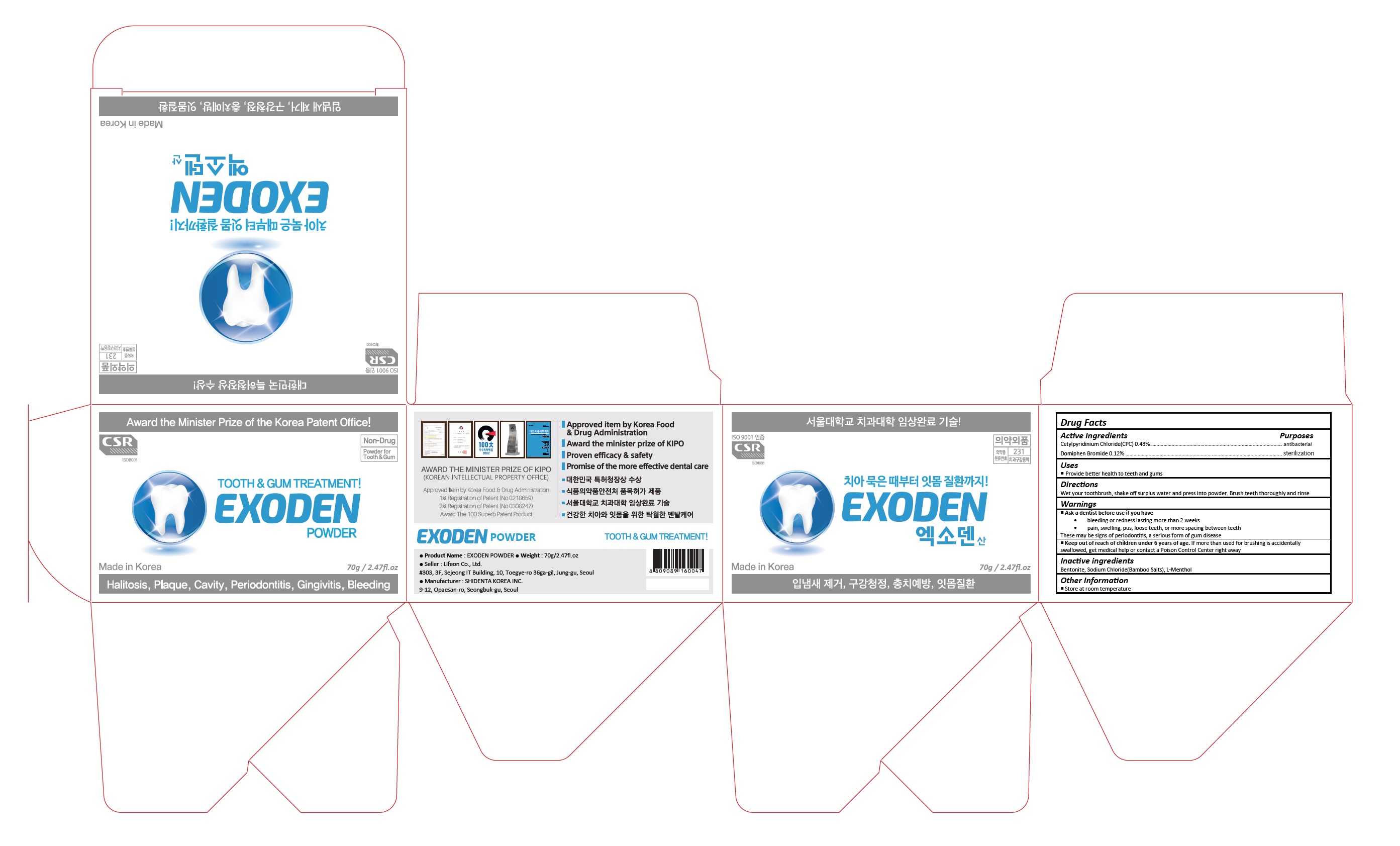 DRUG LABEL: Exoden Powder
NDC: 70602-003 | Form: POWDER
Manufacturer: LIFEON Corp.
Category: otc | Type: HUMAN OTC DRUG LABEL
Date: 20210309

ACTIVE INGREDIENTS: DOMIPHEN BROMIDE 0.12 1/100 g; CETYLPYRIDINIUM CHLORIDE 0.043 g/100 g
INACTIVE INGREDIENTS: BENTONITE; SODIUM CHLORIDE; LEVOMENTHOL

70602-003_Exoden Powder

ACTIVE INGREDIENT

Cetylpyridinium Chloride(CPC) 0.43%
Domiphen Bromide 0.120

PURPOSE

Oral Health Care

INDICATIONS AND USAGE

Provide better health to teeth and gums

DOSAGE AND ADMINISTRATION

Wet your toothbrush, shake off surplus water and press into powder. Brush teeth thoroughly and rinse

WARNINGS

Ask a dentist before use if you have
• bleeding or redness lasting more than 2 weeks
• pain, swelling, pus, loose teeth, or more spacing between teeth
These may be signs of periodontitis, a serious form of gum disease

Keep out of reach of children under 6 years of age. If more than used for brushing is accidentally swallowed, get medical help or contact a Poison Control Center right away

INACTIVE INGREDIENT

Bentonite, Sodium Chloride(Bamboo Salts), L-Menthol